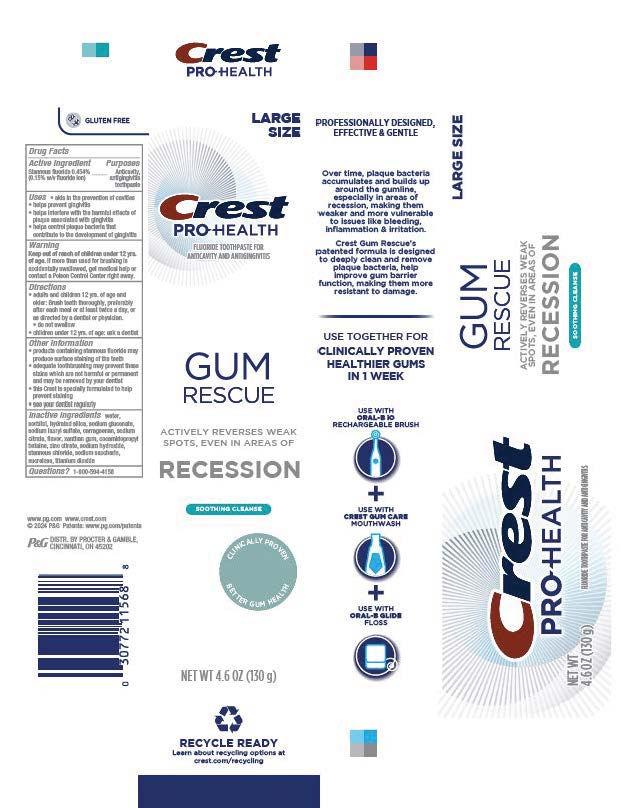 DRUG LABEL: Crest Pro-Health
NDC: 84126-609 | Form: PASTE, DENTIFRICE
Manufacturer: The Procter & Gamble Manufacturing Company
Category: otc | Type: HUMAN OTC DRUG LABEL
Date: 20260106

ACTIVE INGREDIENTS: STANNOUS FLUORIDE 1.5 mg/1 g
INACTIVE INGREDIENTS: GLYCINE; SUCRALOSE; HYDRATED SILICA; SORBITOL; SODIUM CITRATE; COCAMIDOPROPYL BETAINE; WATER; SODIUM LAURYL SULFATE; SODIUM GLUCONATE; CARRAGEENAN; SACCHARIN SODIUM; XANTHAN GUM; ZINC CITRATE; SODIUM HYDROXIDE; STANNOUS CHLORIDE; TITANIUM DIOXIDE

Crest Pro-Health Gum Rescue Pro Soothing Clean

Drug Facts

Active ingredient

Stannous fluoride 0.454% (0.15% w/v fluoride ion)

Purposes

Anticavity, antigingivitis toothpaste

Uses

- aids in the prevention of cavities
- helps prevent gingivitis
- helps interfere with the harmful effects of plaque associated with gingivitis
- helps control plaque bacteria that contribute to the development of gingivitis

Warnings

Keep out of reach of children under 12 yrs.
of age. If more than used for brushing is
accidentally swallowed, get medical help or
contact a Poison Control Center right away.

Directions

- adults and children 12 yrs. of age and
  older: Brush teeth thoroughly, preferably
  after each meal or at least twice a day, or
  as directed by a dentist or physician.
  • do not swallow
  • children under 12 yrs. of age: ask a dentist

Other information

- products containing stannous fluoride may produce surface staining of the teeth
- adequate toothbrushing may prevent these stains which are not harmful or permanent and may be removed by your dentist
- this Crest is specially formulated to help prevent staining
- see your dentist regularly

Inactive ingredients

water, sorbitol, hydrated silica, sodium gluconate, sodium lauryl sulfate, carrageenan, sodium citrate, flavor, xanthan gum, cocamidopropyl betaine, zinc citrate, sodium hydroxide, stannous chloride, sodium saccharin, sucralose, titanium dioxide

Questions?

1-800-594-4158

DISTR. BY PROCTER & GAMBLE,
CINCINNATI, OH 45202

PRINCIPAL DISPLAY PANEL - 130 g Tube Carton

LARGE

SIZE

Crest

PRO-HEALTH

FLUORIDE TOOTHPASTE FOR
ANTICAVITY AND ANTIGINGIVITIS

GUM

RESCUE

ACTIVELY REVERSES WEAK

SPOTS, EVEN IN AREAS OF

RECESSION

SOOTHING CLEANSE

CLINICALLY PROVEN

BETTER GUM HEALTH

NET WT 4.6 OZ (130 g)